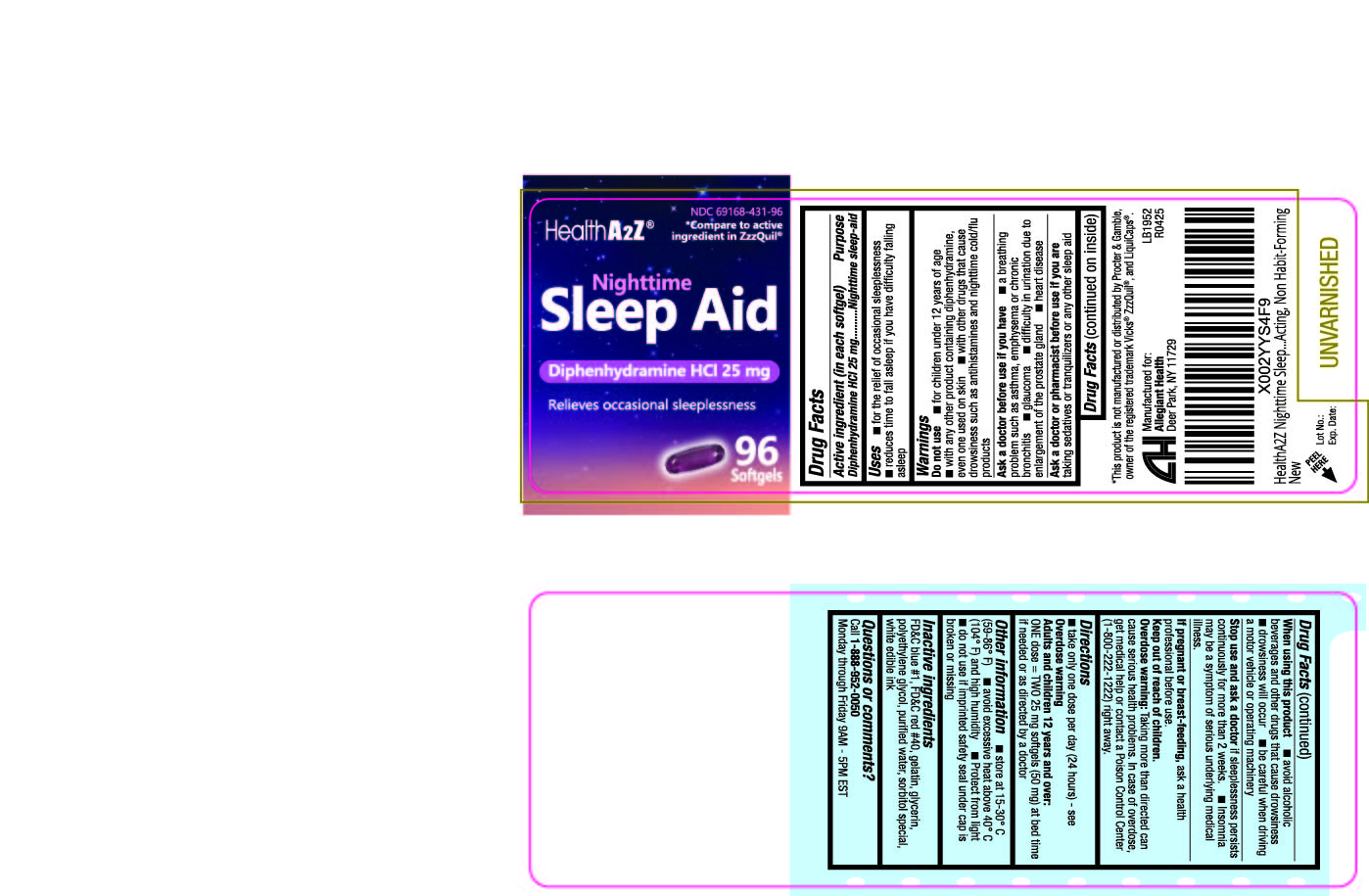 DRUG LABEL: Sleep Aid
NDC: 69168-431 | Form: CAPSULE, LIQUID FILLED
Manufacturer: Allegiant Health
Category: otc | Type: HUMAN OTC DRUG LABEL
Date: 20210830

ACTIVE INGREDIENTS: DIPHENHYDRAMINE HYDROCHLORIDE 25 mg/1 1
INACTIVE INGREDIENTS: FD&C BLUE NO. 1; FD&C RED NO. 40; GELATIN; GLYCERIN; POLYETHYLENE GLYCOL, UNSPECIFIED; WATER; SORBITOL

431 - Sleep Aid Diphenhydramine HCl 25mg

Active ingredient(s)

Diphenhydramine HCl 25 mg

Purpose

Nighttime sleep-aid

Use(s)

- for the relief of occasional sleeplessness
- reduces time to fall asleep if you have difficulty falling asleep

Warnings

Do not use

- for children under 12 years of age
- with any other product containing diphenhydramine, even one used on skin
- with other drugs that cause drowsiness such as antihistamines and nighttime cold/flu products

Ask a doctor before use if

- a breathing problem such as asthma, emphysema or chronic bronchitis
- glaucoma
- difficulty in urination due to enlargement of the prostate gland
- heart disease

Ask a doctor or pharmacist before use if

you are taking sedatives or tranquilizers or any other sleep aid

When using this product

- avoid alcoholic beverages and other drugs that cause drowsiness
- drowsiness will occur
- be careful when driving a motor vehicle or operating machinery

Stop use and ask a doctor if

if sleeplessness persists continuously for more than 2 weeks.

- Insomnia may be a symptom of serious underlying medical illness.

If Pregnant or Breastfeeding,

ask a health professional before use.

Keep out of reach of children

Overdose warning: Taking more than directed can cause serious health problems. In case of overdose, get medical
help or contact a Poison Control Center (1-800-222-1222) right away.

Directions

take only one dose per day (24 hours) - see Overdose warning

Adults and children 12 years and over: ONE dose = TWO 25 mg softgels (50 mg) at bed time if needed or as directed by a doctor

Other information

Do not use if blister unit is torn or open.

Do not use if imprinted safety seal under cap is broken or missing.

Storage

- store at 15-30° C (59-86° F)
- avoid excessive heat above 40° C (104° F) and high humidity
- Protect from light

Inactive ingredients

FD&C blue #1, FD&C red #40, gelatin, glycerin, polyethylene glycol, purified water, sorbitol special, white edible ink

Questions

Call 1-888-952-0050 Monday through Friday 9AM - 5PM EST

Principal Display Panel

Sleep Aid